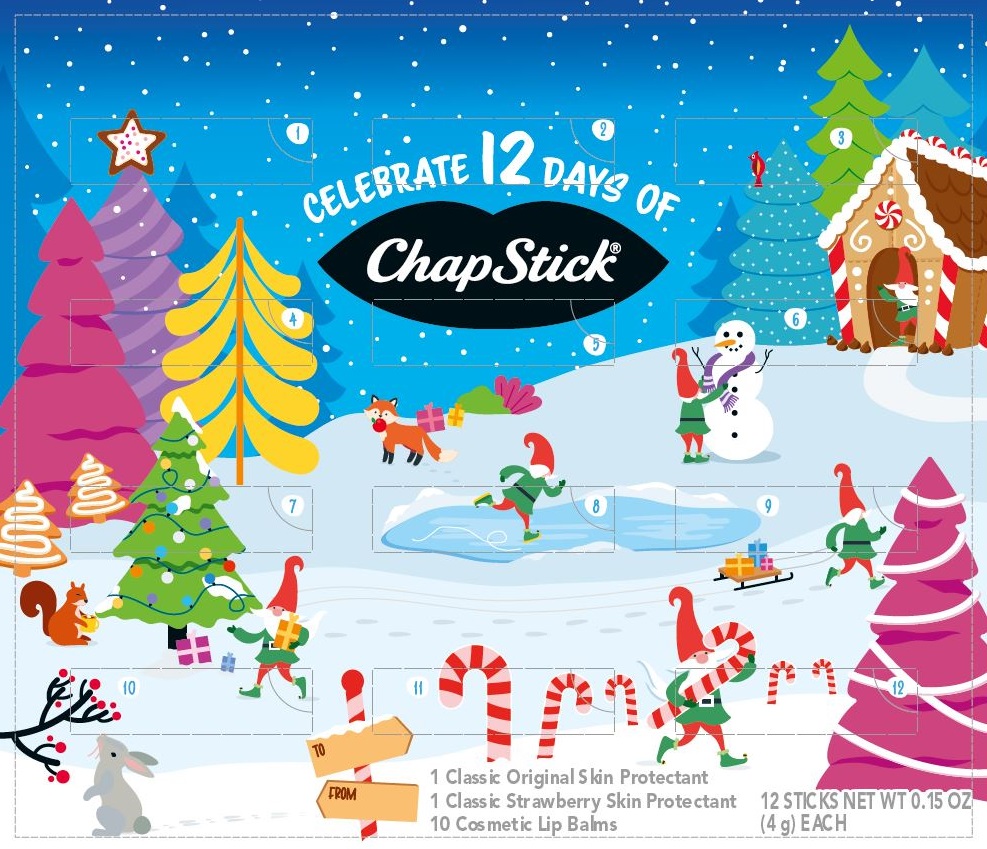 DRUG LABEL: Chapstick
NDC: 0573-0804 | Form: KIT | Route: TOPICAL
Manufacturer: Haleon US Holdings LLC
Category: otc | Type: HUMAN OTC DRUG LABEL
Date: 20240411

ACTIVE INGREDIENTS: PETROLATUM 450 mg/1 g; PETROLATUM 450 mg/1 g
INACTIVE INGREDIENTS: CAMPHOR (NATURAL); CARNAUBA WAX; CETYL ALCOHOL; ISOPROPYL MYRISTATE; LANOLIN; LIGHT MINERAL OIL; OCTYLDODECANOL; OLEYL ALCOHOL; PARAFFIN; PHENYL TRIMETHICONE; D&C RED NO. 6; TITANIUM DIOXIDE; WHITE WAX; FD&C YELLOW NO. 5; ARACHIDYL PROPIONATE; CAMPHOR (NATURAL); CARNAUBA WAX; CETYL ALCOHOL; ISOPROPYL MYRISTATE; LANOLIN; LEMON OIL, COLD PRESSED; LIGHT MINERAL OIL; MALTOL; OCTYLDODECANOL; PARAFFIN; PHENYL TRIMETHICONE; D&C RED NO. 6; TITANIUM DIOXIDE; SACCHARIN; WHITE WAX

Drug Facts

Classic Original | Strawberry

Active ingredient

White Petrolatum 45%

Purpose

Skin Protectant

Uses

- helps prevent and temporarily protects chafed, chapped or cracked lips
- helps prevent and protect from the drying effects of wind and cold weather

Warnings

For external use only

Inactive ingredients (Original)

arachidyl propionate, camphor, carnauba wax, cetyl alcohol, fragrance, isopropyl lanolate, isopropyl myristate, lanolin, light mineral oil, octyldodecanol, oleyl alcohol, paraffin, phenyl trimethicone, red 6 lake, titanium dioxide, white wax, yellow 5 lake

Inactive ingredients (Strawberry)

arachidyl propionate, camphor, carnauba wax, cetyl alcohol, fragrance, isopropyl lanolate, isopropyl myristate, lanolin, lemon oil, light mineral oil, maltol, octyldodecanol, paraffin, phenyl trimethicone, red 6 lake, saccharin, white wax

Cosmetic Lip Balms

Vanilla Mint

Ingredients:petrolatum, paraffin, mineral oil, octyldodecanol, bis-diglyceryl polyacyladipate-2, caprylic/capric triglyceride, arachidyl propionate, phenyl trimethicone, beeswax, copernicia cerifera (carnauba) wax, isopropyl myristate, flavor, cetyl alcohol, lecithin (soy), ethyl alcohol, saccharin

Sugar Cookie

Ingredients:petrolatum, paraffin, mineral oil, octyldodecanol, bis-diglyceryl polyacyladipate-2, arachidyl propionate, phenyl trimethicone, beeswax, caprylic/capric triglyceride, flavor, copernicia cerifera (carnauba) wax, isopropyl myristate, cetyl alcohol, benzyl benzoate, triacetin, saccharin

Cotton Candy

Ingredients:petrolatum, paraffin, mineral oil, octyldodecanol, bis-diglyceryl polyacyladipate-2, arachidyl propionate, phenyl trimethicone, beeswax, benzyl benzoate, copernicia cerifera (carnauba) wax, isopropyl myristate, cetyl alcohol, lecithin (soy), flavor, saccharin, synthetic wax, blue 1 lake, isopropyl titanium triisostearate

Green Apple

Ingredients:petrolatum, paraffin, mineral oil, octyldodecanol, bis-diglyceryl polyacyladipate-2, arachidyl propionate, phenyl trimethicone, beeswax, artificial flavors, copernicia cerifera (carnauba) wax, isopropyl myristate, cetyl alcohol, lecithin (soy), saccharin, synthetic wax, yellow 5 lake, benzyl alcohol, caprylic/ capric triglycerides, titanium dioxide, blue 1 lake, isopropyl titanium triisostearate

Clover Honey

Ingredients:petrolatum, paraffin, mineral oil, octyldodecanol, canola oil, bis-diglyceryl polyacyladipate-2, arachidyl propionate, phenyl trimethicone, beeswax, copernicia cerifera (carnauba) wax, isopropyl myristate, cetyl alcohol, lecithin (soy), flavor, saccharin, synthetic wax, iron oxides, isopropyl titanium triisostearate

Vanilla Icing

Ingredients:petrolatum, paraffin, mineral oil, octyldodecanol, bis-diglyceryl polyacyladipate-2, caprylic/capric triglyceride, phenyl trimethicone, arachidyl propionate, beeswax, isopropyl myristate, copernicia cerifera (carnauba) wax, lecithin (soy), cetyl alcohol, flavor, triacetin, benzyl benzoate, saccharin, titanium dioxide, synthetic wax, isopropyl titanium triisostearate

Cake Batter

Ingredients:petrolatum, paraffin, mineral oil, octyldodecanol, bis-diglyceryl polyacyladipate-2, caprylic/capric triglyceride, phenyl trimethicone, arachidyl propionate, beeswax, isopropyl myristate, copernicia cerifera (carnauba) wax, lecithin (soy), cetyl alcohol, flavor, triacetin, benzyl benzoate, saccharin, titanium dioxide, synthetic wax, isopropyl titanium triisostearate

Graham Cracker

Ingredients:petrolatum, paraffin, mineral oil, octyldodecanol, caprylic/capric triglyceride, bis-diglyceryl polyacyladipate-2, phenyl trimethicone, arachidyl propionate, beeswax, isopropyl myristate, copernicia cerifera (carnauba) wax, lecithin (soy), cetyl alcohol, flavor, titanium dioxide, synthetic wax, saccharin, iron oxides, benzyl benzoate, isopropyl titanium triisostearate

Milk Chocolate

Ingredients:petrolatum, paraffin, mineral oil, octyldodecanol, bis-diglyceryl polyacyladipate-2, phenyl trimethicone, arachidyl propionate, beeswax, caprylic/capric triglyceride, triacetin, copernicia cerifera (carnauba) wax, isopropyl myristate, flavor, cetyl alcohol, lecithin (soy), titanium dioxide, synthetic wax, iron oxides, saccharin, benzyl benzoate, isopropyl titanium triisostearate

Candy Cane

Ingredients:petrolatum, paraffin, mineral oil, octyldodecanol, bis-diglyceryl polyacyladipate-2, flavor, arachidyl propionate, phenyl trimethicone, beeswax, copernicia cerifera (carnauba) wax, isopropyl myristate, cetyl alcohol, titanium dioxide, synthetic wax, saccharin, canola oil, isopropyl titanium triisostearate

Additional Information

Dist. by: GSK CH, Warren, NJ 07059

For most recent product information, visit www.chapstick.com

Questions or Comments?1-800-245-1040

Trademarks owned or licensed by GSK.

©2023 GSK or licensor.

Paraben Free

PRINCIPAL DISPLAY PANEL

Celebrate 12 Days of

ChapStick®

1 Classic Original Skin Protectant

1 Classic Strawberry Skin Protectant

10 Cosmetic Lip Balms

12 STICKS NET WT 0.15 OZ

(4 g) EACH

203529 – Front